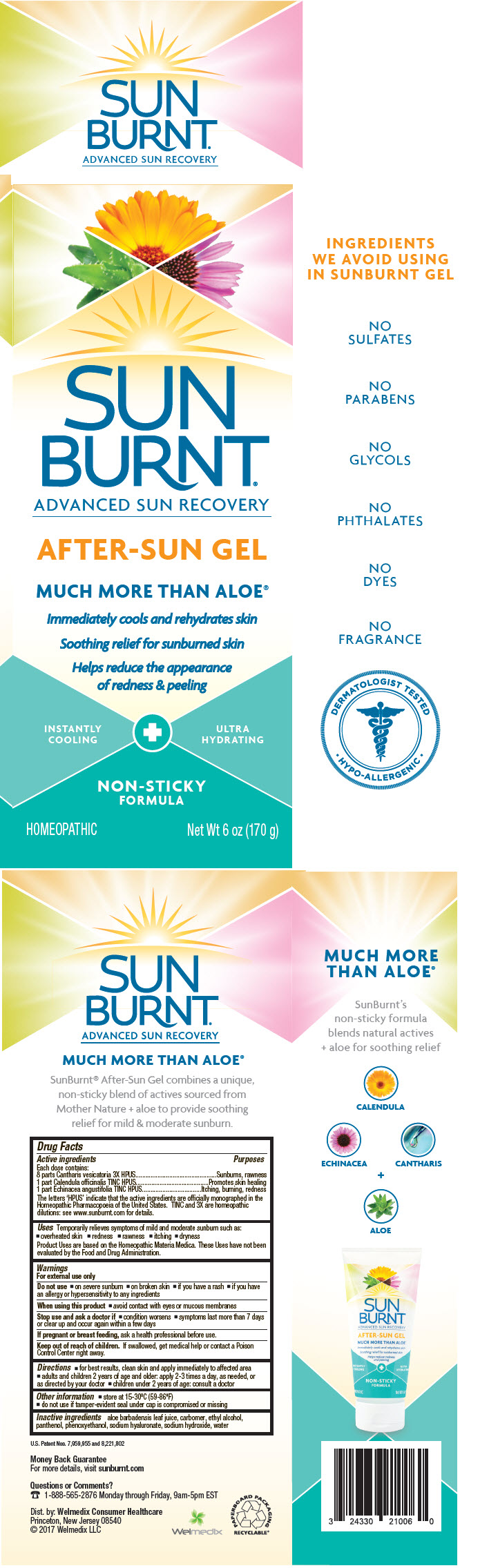 DRUG LABEL: SunBurnt Advanced After-Sun
NDC: 24330-210 | Form: GEL
Manufacturer: Welmedix LLC
Category: homeopathic | Type: HUMAN OTC DRUG LABEL
Date: 20180320

ACTIVE INGREDIENTS: CALENDULA OFFICINALIS FLOWER 1 [hp_Q]/0.1 g; ECHINACEA ANGUSTIFOLIA 1 [hp_Q]/0.1 g; LYTTA VESICATORIA 3 [hp_X]/0.1 g
INACTIVE INGREDIENTS: ALOE VERA LEAF; CARBOMER COPOLYMER TYPE A (ALLYL PENTAERYTHRITOL CROSSLINKED); ALCOHOL; PANTHENOL; PHENOXYETHANOL; WATER; HYALURONATE SODIUM; SODIUM HYDROXIDE

SunBurnt® Advanced After-Sun Gel

Drug Facts

ACTIVE INGREDIENT

PURPOSE

Active ingredients | Purposes
Each dose contains:
8 parts Cantharis vesicatoria 3X HPUS | Sunburns, rawness
1 part Calendula officinalis TINC HPUS | Promotes skin healing
1 part Echinacea angustifolia TINC HPUS | Itching, burning, redness
The letters 'HPUS' indicate that the active ingredients are officially monographed in the Homeopathic Pharmacopoeia of the United States. TINC and 3X are homeopathic dilutions: see www.sunburnt.com for details.

Uses

Temporarily relieves symptoms of mild and moderate sunburn such as:

- overheated skin
- redness
- rawness
- itching
- dryness

Product Uses are based on the Homeopathic Materia Medica. These Uses have not been evaluated by the Food and Drug Administration.

Warnings

For external use only

Do not use

- on severe sunburn
- on broken skin
- if you have a rash
- if you have an allergy or hypersensitivity to any ingredients

When using this product

- avoid contact with eyes or mucous membranes

Stop use and ask a doctor if

- condition worsens
- symptoms last more than 7 days or clear up and occur again within a few days

PREGNANCY OR BREAST FEEDING

If pregnant or breast feeding, ask a health professional before use.

Keep out of reach of children. If swallowed, get medical help or contact a Poison Control Center right away.

Directions

- for best results, clean skin and apply immediately to affected area
- adults and children 2 years of age and older: apply 2-3 times a day, as needed, or as directed by your doctor
- children under 2 years of age: consult a doctor

Other information

- store at 15-30ºC (59-86ºF)
- do not use if tamper-evident seal under cap is compromised or missing

Inactive ingredients

aloe barbadensis leaf juice, carbomer, ethyl alcohol, panthenol, phenoxyethanol, sodium hyaluronate, sodium hydroxide, water

Questions or Comments?

1-888-565-2876 Monday through Friday, 9am-5pm EST

Dist. by: Welmedix Consumer Healthcare
Princeton, New Jersey 08540

PRINCIPAL DISPLAY PANEL - 170 g Tube Carton

SUN
BURNT®
ADVANCED SUN RECOVERY

AFTER-SUN GEL

MUCH MORE THAN ALOE®

Immediately cools and rehydrates skin

Soothing relief for sunburned skin

Helps reduce the appearance
of redness & peeling

INSTANTLY
COOLING
ULTRA
HYDRATING
NON-STICKY
FORMULA

HOMEOPATHIC
Net Wt 6 oz (170 g)